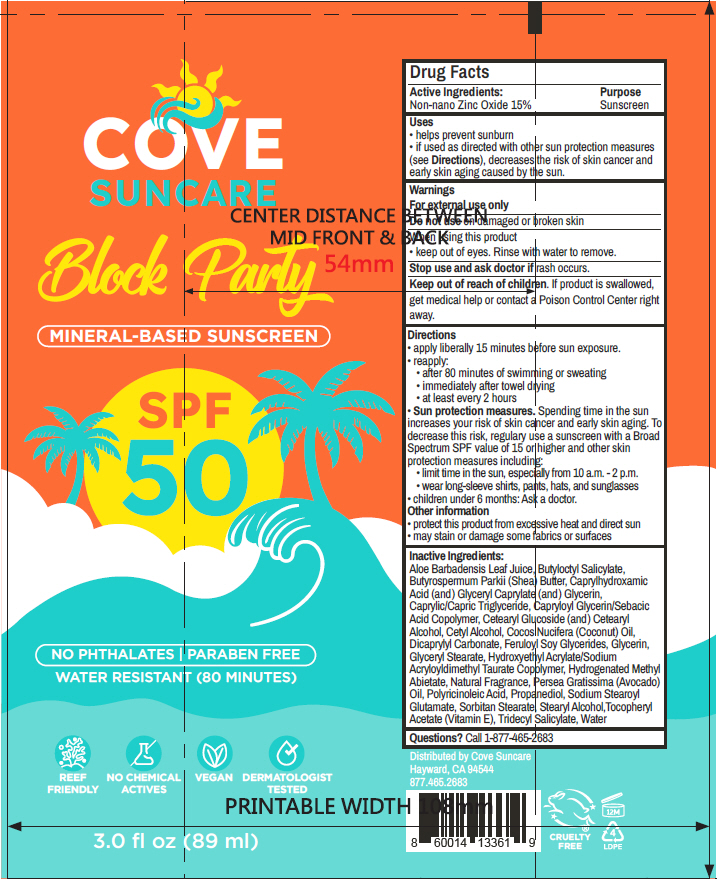 DRUG LABEL: Block Party SPF-50
NDC: 85753-102 | Form: LOTION
Manufacturer: Cove Suncare LLC
Category: otc | Type: HUMAN OTC DRUG LABEL
Date: 20251008

ACTIVE INGREDIENTS: Zinc Oxide 15 g/100 mL
INACTIVE INGREDIENTS: Butyloctyl Salicylate; Tridecyl Salicylate; Aloe Vera Leaf Juice; Medium-Chain Triglycerides; Propanediol; Glyceryl Monostearate; Hydrogenated Methyl Abietate; Sorbitan Monostearate; Capryloyl Glycerin/Sebacic Acid Copolymer (2000 Mpa.S); Cetearyl Glucoside; Cetostearyl Alcohol; Glycerin; Dicaprylyl Carbonate; Avocado Oil; Hydroxyethyl Acrylate/Sodium Acryloyldimethyl Taurate Copolymer (100000 Mpa.S At 1.5%); Caprylhydroxamic Acid; Glyceryl Monocaprylate; Coconut Oil; Cetyl Alcohol; Stearyl Alcohol; Sodium Stearoyl Glutamate; .Alpha.-Tocopherol Acetate; Shea Butter

Block Party SPF-50

Drug Facts

Active Ingredients

Non-nano Zinc Oxide 15%

Purpose

Sunscreen

Uses

- helps prevent sunburn
- if used as directed with other sun protection measures (see Directions), decreases the risk of skin cancer and early skin aging caused by the sun.

Warnings

For external use only

Do not use on damaged or broken skin

When using this product

- keep out of eyes. Rinse with water to remove.

Stop use and ask doctor if rash occurs.

Keep out of reach of children. If product is swallowed, get medical help or contact a Poison Control Center right away.

Directions

- apply liberally 15 minutes before sun exposure.
- reapply:
  - after 80 minutes of swimming or sweating
  - immediately after towel drying
  - at least every 2 hours
- Sun protection measures. Spending time in the sun increases your risk of skin cancer and early skin aging. To decrease this risk, regulary use a sunscreen with a Broad Spectrum SPF value of 15 or higher and other skin protection measures including:
  - limit time in the sun, especially from 10 a.m. - 2 p.m.
  - wear long-sleeve shirts, pants, hats, and sunglasses
- children under 6 months: Ask a doctor.

Other information

- protect this product from excessive heat and direct sun
- may stain or damage some fabrics or surfaces

Inactive Ingredients

Aloe Barbadensis Leaf Juice, Butyloctyl Salicylate, Butyrospermum Parkii (Shea) Butter, Caprylhydroxamic Acid (and) Glyceryl Caprylate (and) Glycerin, Caprylic/Capric Triglyceride, Capryloyl Glycerin/Sebacic Acid Copolymer, Cetearyl Glucoside (and) Cetearyl Alcohol, Cetyl Alcohol, Cocos Nucifera (Coconut) Oil, Dicaprylyl Carbonate, Feruloyl Soy Glycerides, Glycerin, Glyceryl Stearate, Hydroxyethyl Acrylate/Sodium Acryloyldimethyl Taurate Copolymer, Hydrogenated Methyl Abietate, Natural Fragrance, Persea Gratissima (Avocado) Oil, Polyricinoleic Acid, Propanediol, Sodium Stearoyl Glutamate, Sorbitan Stearate, Stearyl Alcohol,Tocopheryl Acetate (Vitamin E), Tridecyl Salicylate, Water

Questions?

Call 1-877-465-2683

Distributed by Cove Suncare
Hayward, CA 94544

PRINCIPAL DISPLAY PANEL - 89 ml Tube Label

COVE
SUNCARE

Block Party

MINERAL-BASED SUNSCREEN

SPF
50

NO PHTHALATES | PARABEN FREE
WATER RESISTANT (80 MINUTES)

REEF
FRIENDLY

NO CHEMICAL
ACTIVES

VEGAN

DERMATOLOGIST
TESTED

3.0 fl oz (89 ml)